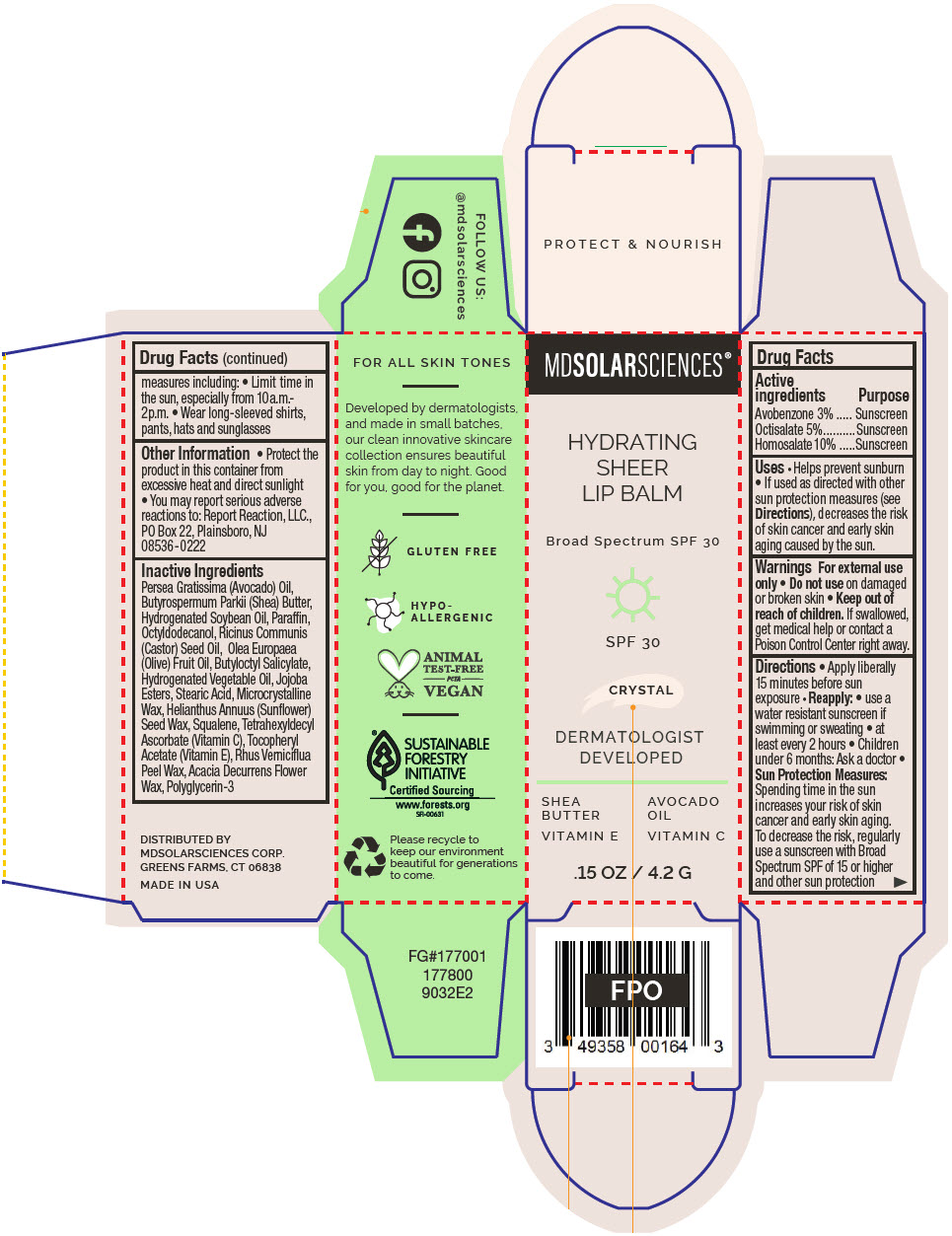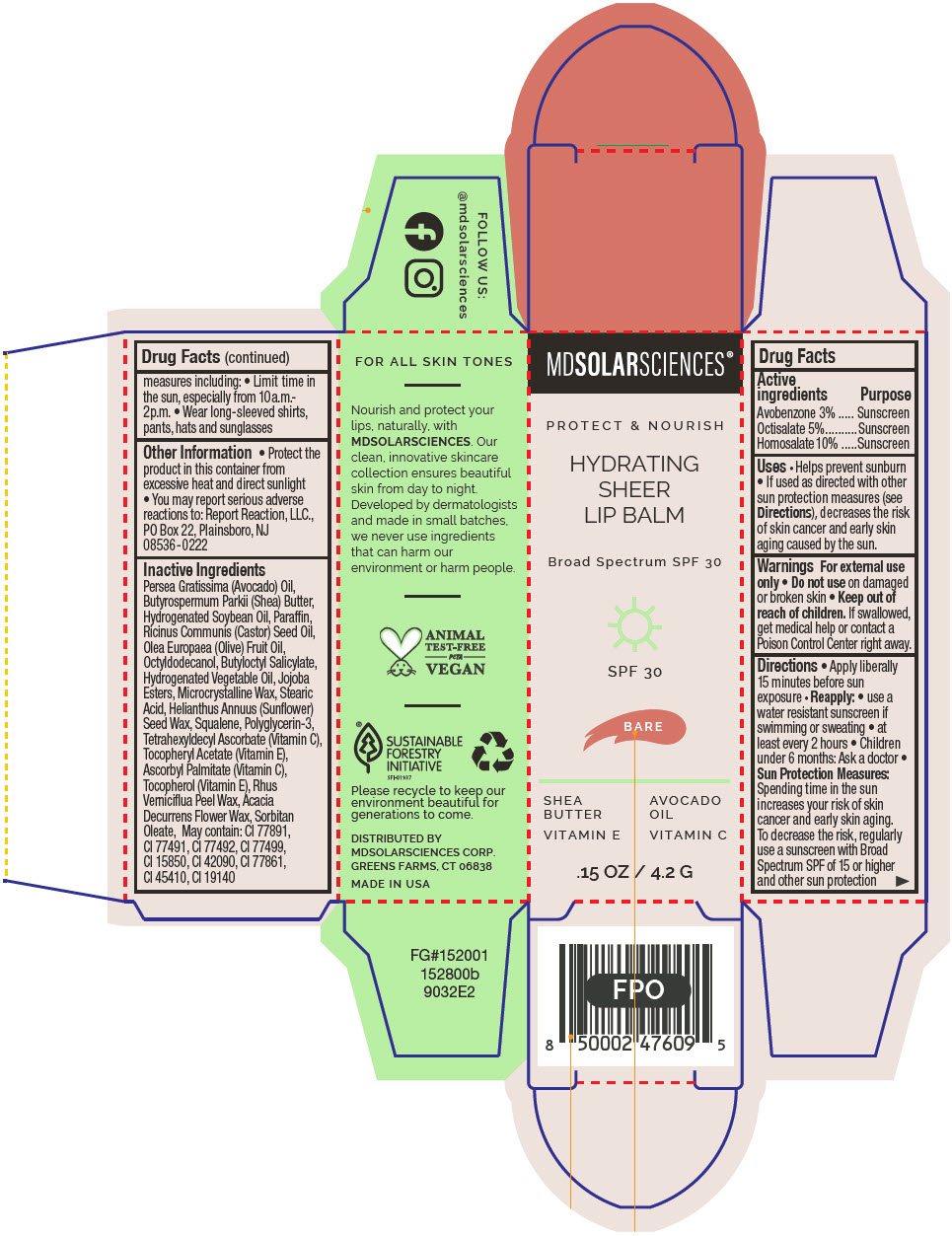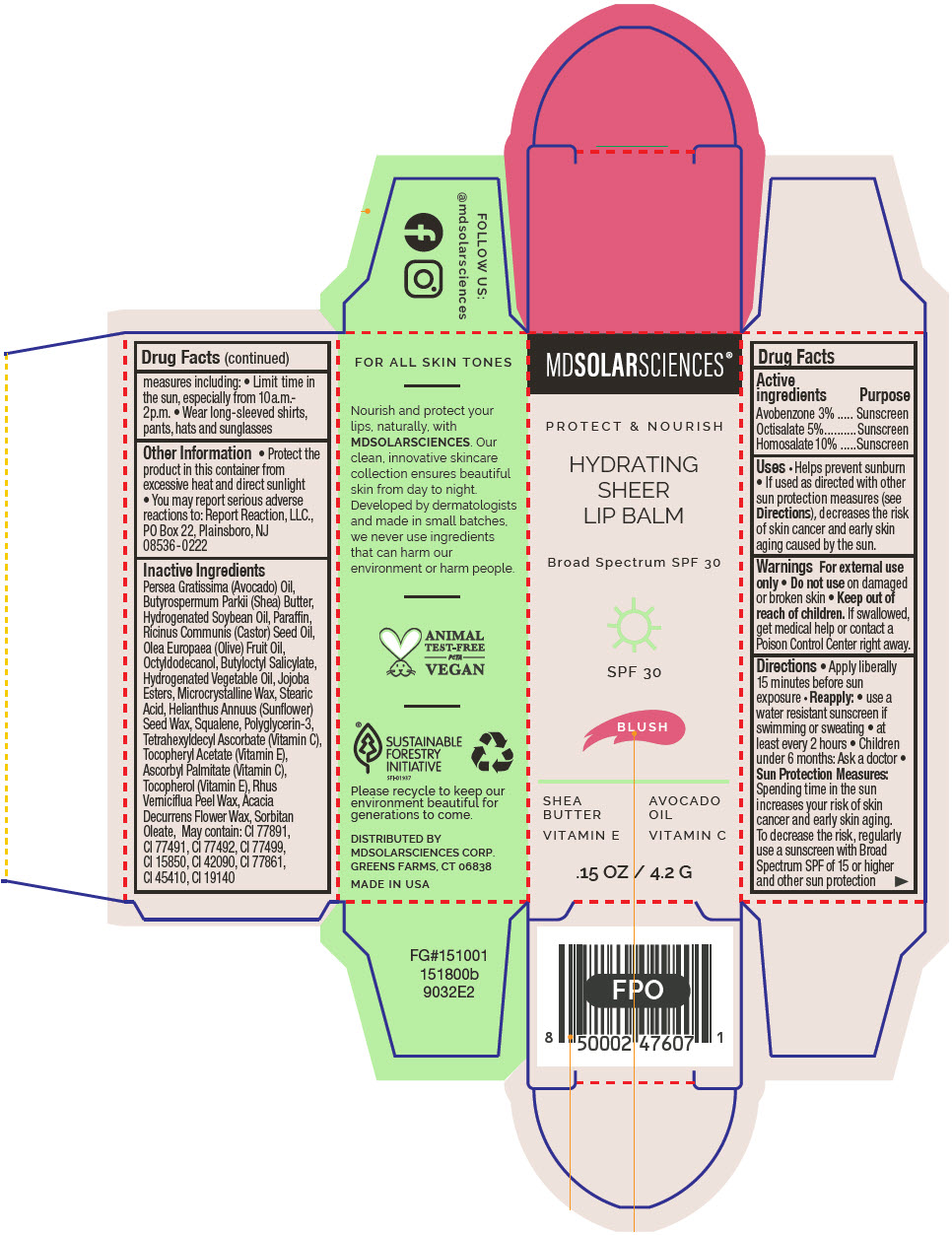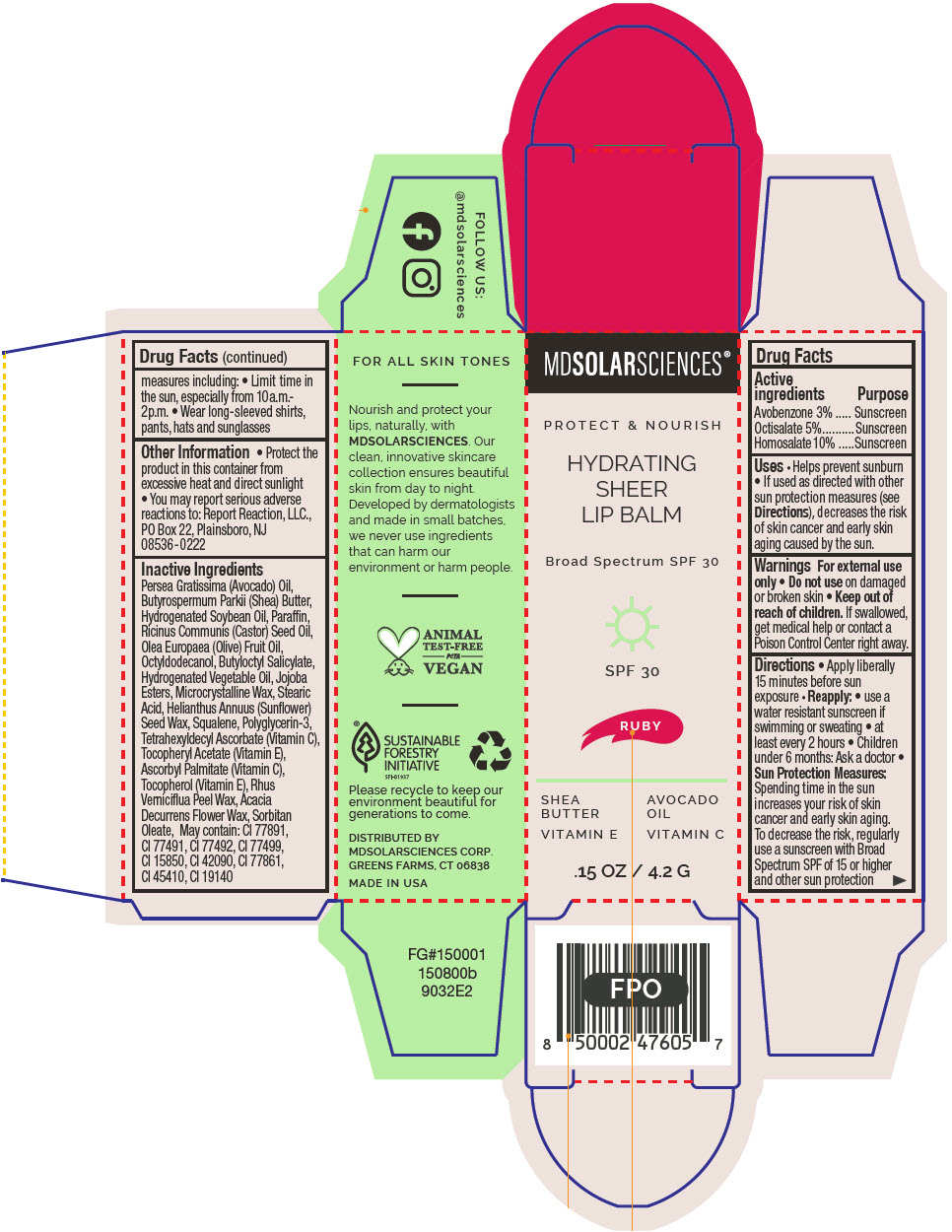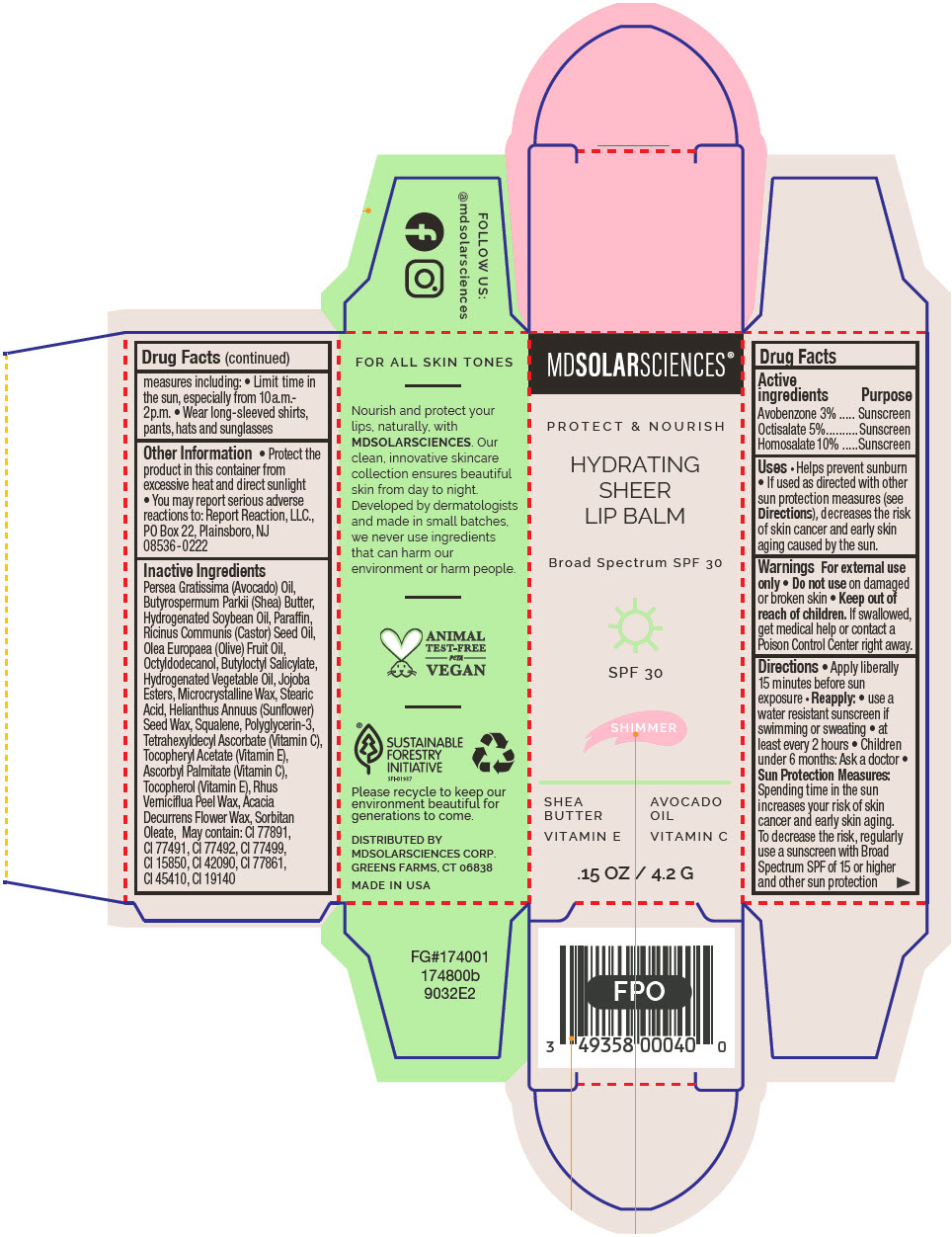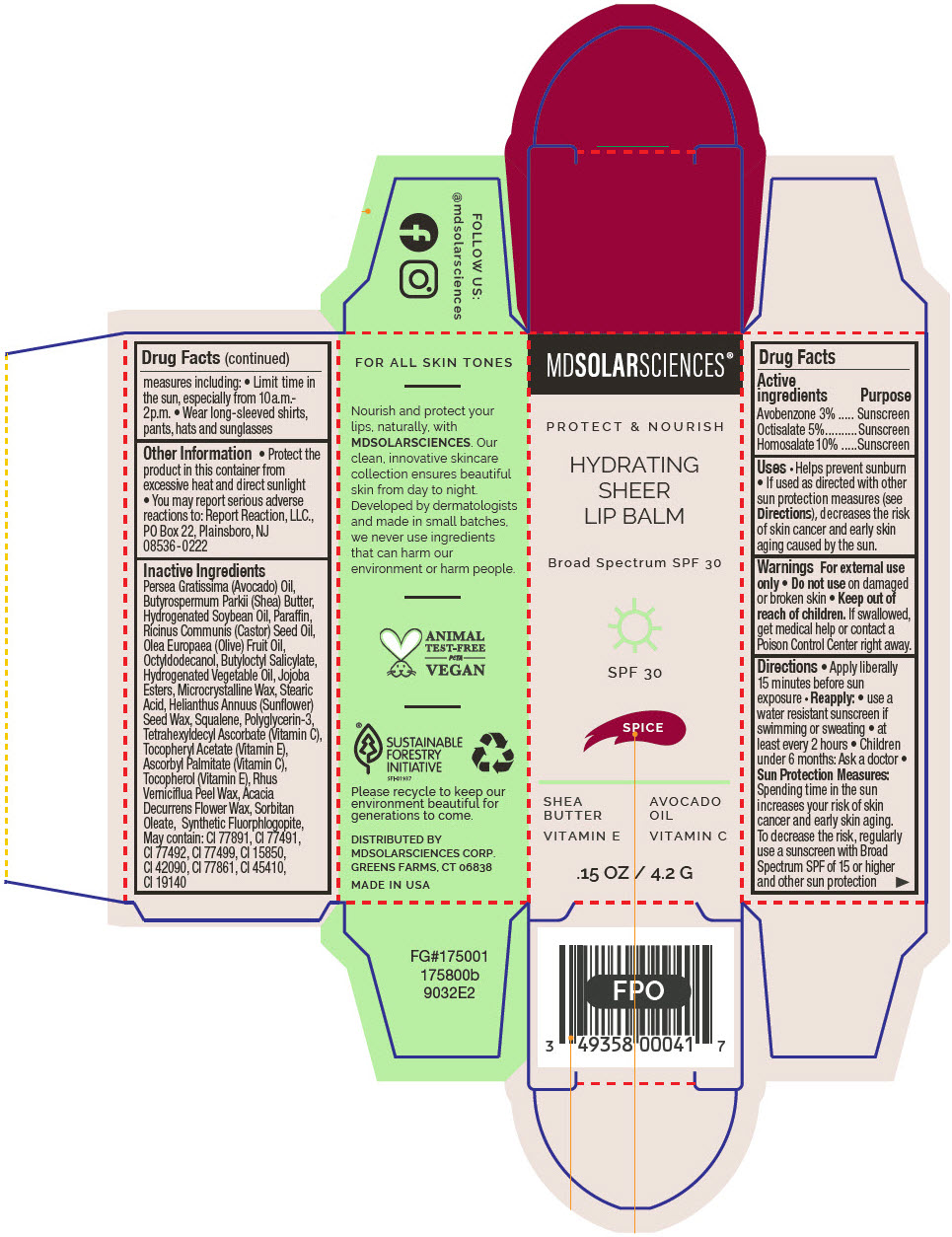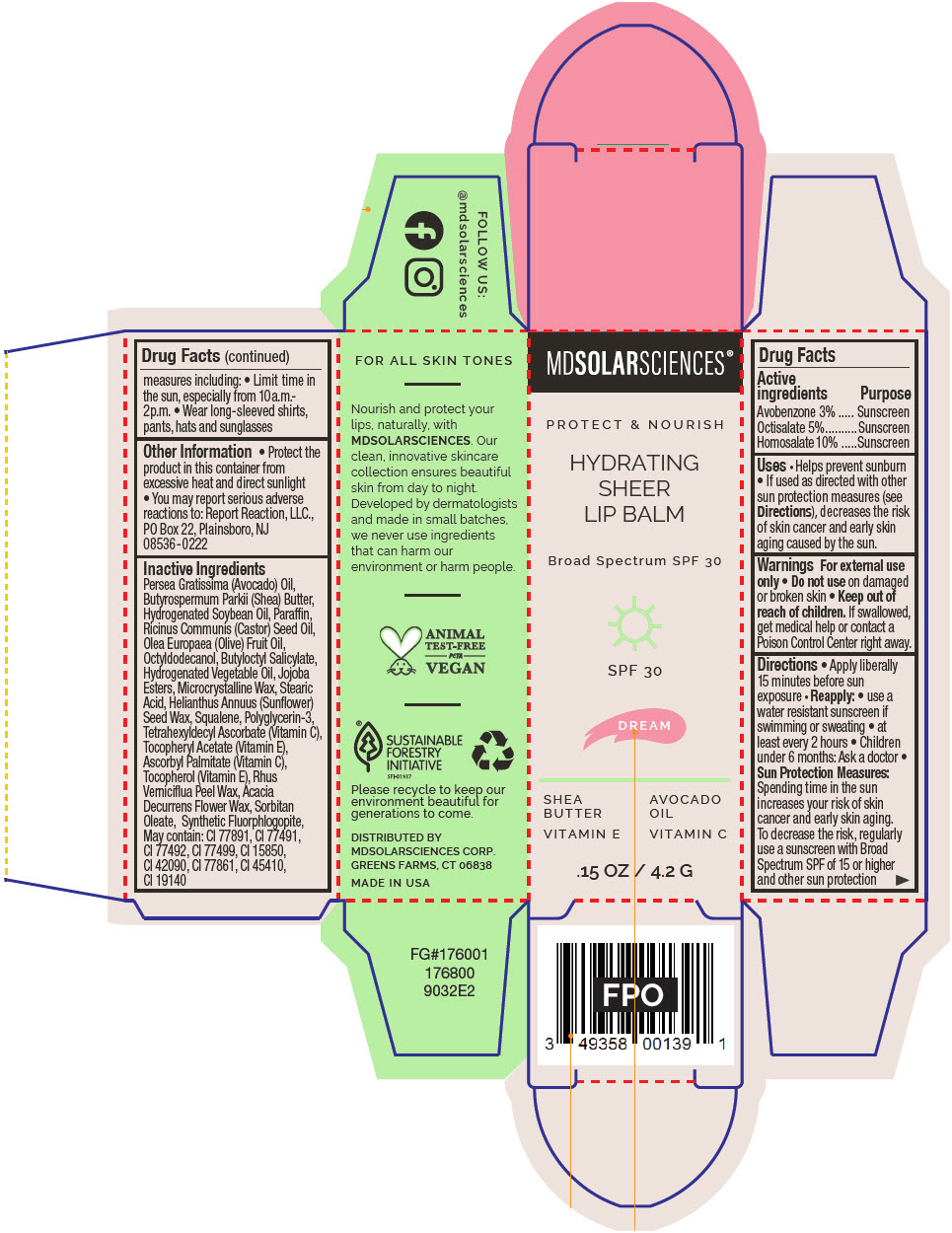 DRUG LABEL: Hydrating Sheer Lip Balm SPF 30 -Crystal
NDC: 49358-600 | Form: LIPSTICK
Manufacturer: MDSolarSciences
Category: otc | Type: HUMAN OTC DRUG LABEL
Date: 20250605

ACTIVE INGREDIENTS: AVOBENZONE 30 mg/1 g; OCTISALATE 50 mg/1 g; HOMOSALATE 100 mg/1 g
INACTIVE INGREDIENTS: AVOCADO OIL; SHEA BUTTER; HYDROGENATED SOYBEAN OIL; PARAFFIN; OCTYLDODECANOL; CASTOR OIL; OLIVE OIL; BUTYLOCTYL SALICYLATE; CORN OIL; HYDROGENATED JOJOBA OIL, RANDOMIZED; STEARIC ACID; MICROCRYSTALLINE WAX; HELIANTHUS ANNUUS SEED WAX; SQUALANE; TETRAHEXYLDECYL ASCORBATE; .ALPHA.-TOCOPHEROL ACETATE; TOXICODENDRON VERNICIFLUUM FRUIT RIND WAX; ACACIA DECURRENS FLOWER WAX; POLYGLYCERIN-3

Hydrating Sheer Lip Balm SPF 30
Broad Spectrum SPF 30 UVA-UVB Sunscreen

Drug Facts

ACTIVE INGREDIENT

Active ingredients | Purpose
Avobenzone 3% | Sunscreen
Octisalate 5% | Sunscreen
Homosalate 10% | Sunscreen

Uses

- Helps prevent sunburn
- If used as directed with other sun protection measures (see Directions), decreases the risk of skin cancer and early skin aging caused by the sun.

Warnings

For external use only

- Do not useon damaged or broken skin

- Keep out of reach of children.If swallowed, get medical help or contact a Poison Control Center right away.

Directions

- Apply liberally 15 minutes before sun exposure
- Reapply:
  - use a water resistant sunscreen if swimming or sweating
  - at least every 2 hours
- Children under 6 months: Ask a doctor
- Sun Protection Measures:Spending time in the sun increases your risk of skin cancer and early skin aging.
  To decrease the risk, regularly use a sunscreen with Broad Spectrum SPF of 15 or higher and other sun protection measures including:
  - Limit time in the sun, especially from 10a.m.- 2p.m.
  - Wear long-sleeved shirts, pants, hats and sunglasses

Other Information

- Protect the product in this container from excessive heat and direct sunlight
- You may report serious adverse reactions to: Report Reaction, LLC., PO Box 22, Plainsboro, NJ 08536-0222

Inactive Ingredients

Persea Gratissima (Avocado) Oil, Butyrospermum Parkii (Shea) Butter, Hydrogenated Soybean Oil, Paraffin, Ricinus Communis (Castor) Seed Oil, Olea Europaea (Olive) Fruit Oil, Octyldodecanol, Butyloctyl Salicylate, Hydrogenated Vegetable Oil, Jojoba Esters, Microcrystalline Wax, Stearic Acid, Helianthus Annuus (Sunflower) Seed Wax, Squalene, Polyglycerin-3, Tetrahexyldecyl Ascorbate (Vitamin C), Tocopheryl Acetate (Vitamin E), Ascorbyl Palmitate (Vitamin C), Tocopherol (Vitamin E), Rhus Verniciflua Peel Wax, Acacia Decurrens Flower Wax, Sorbitan Oleate, Synthetic Fluorphlogopite, May contain: CI 77891, CI 77491, CI 77492, CI 77499, CI 15850, CI 42090, CI 77861, CI 45410, CI 19140

DISTRIBUTED BY
MDSOLARSCIENCES CORP.
GREENS FARMS, CT 06838

PRINCIPAL DISPLAY PANEL - 4.2 G Applicator Carton - Crystal

MDSOLARSCIENCES®

HYDRATING
SHEER
LIP BALM

Broad Spectrum SPF 30

SPF 30

CRYSTAL

DERMATOLOGIST
DEVELOPED

SHEA
BUTTER
VITAMIN E

AVOCADO
OIL
VITAMIN C

.15 OZ / 4.2 G

PRINCIPAL DISPLAY PANEL - 4.2 G Applicator Carton - Bare

MDSOLARSCIENCES®

PROTECT & NOURISH

HYDRATING
SHEER
LIP BALM

Broad Spectrum SPF 30

SPF 30

BARE

SHEA
BUTTER
VITAMIN E

AVOCADO
OIL
VITAMIN C

.15 OZ / 4.2 G

PRINCIPAL DISPLAY PANEL - 4.2 G Applicator Carton - Blush

MDSOLARSCIENCES®

PROTECT & NOURISH

HYDRATING
SHEER
LIP BALM

Broad Spectrum SPF 30

SPF 30

BLUSH

SHEA
BUTTER
VITAMIN E

AVOCADO
OIL
VITAMIN C

.15 OZ / 4.2 G

PRINCIPAL DISPLAY PANEL - 4.2 G Applicator Carton - Ruby

MDSOLARSCIENCES®

PROTECT & NOURISH

HYDRATING
SHEER
LIP BALM

Broad Spectrum SPF 30

SPF 30

RUBY

SHEA
BUTTER
VITAMIN E

AVOCADO
OIL
VITAMIN C

.15 OZ / 4.2 G

PRINCIPAL DISPLAY PANEL - 4.2 G Applicator Carton - Shimmer

MDSOLARSCIENCES®

PROTECT & NOURISH

HYDRATING
SHEER
LIP BALM

Broad Spectrum SPF 30

SPF 30

SHIMMER

SHEA
BUTTER
VITAMIN E

AVOCADO
OIL
VITAMIN C

.15 OZ / 4.2 G

PRINCIPAL DISPLAY PANEL - 4.2 G Applicator Carton - Spice

MDSOLARSCIENCES®

PROTECT & NOURISH

HYDRATING
SHEER
LIP BALM

Broad Spectrum SPF 30

SPF 30

SPICE

SHEA
BUTTER
VITAMIN E

AVOCADO
OIL
VITAMIN C

.15 OZ / 4.2 G

PRINCIPAL DISPLAY PANEL - 4.2 G Applicator Carton - Dream

MDSOLARSCIENCES®

PROTECT & NOURISH

HYDRATING
SHEER
LIP BALM

Broad Spectrum SPF 30

SPF 30

DREAM

SHEA
BUTTER
VITAMIN E

AVOCADO
OIL
VITAMIN C

.15 OZ / 4.2 G